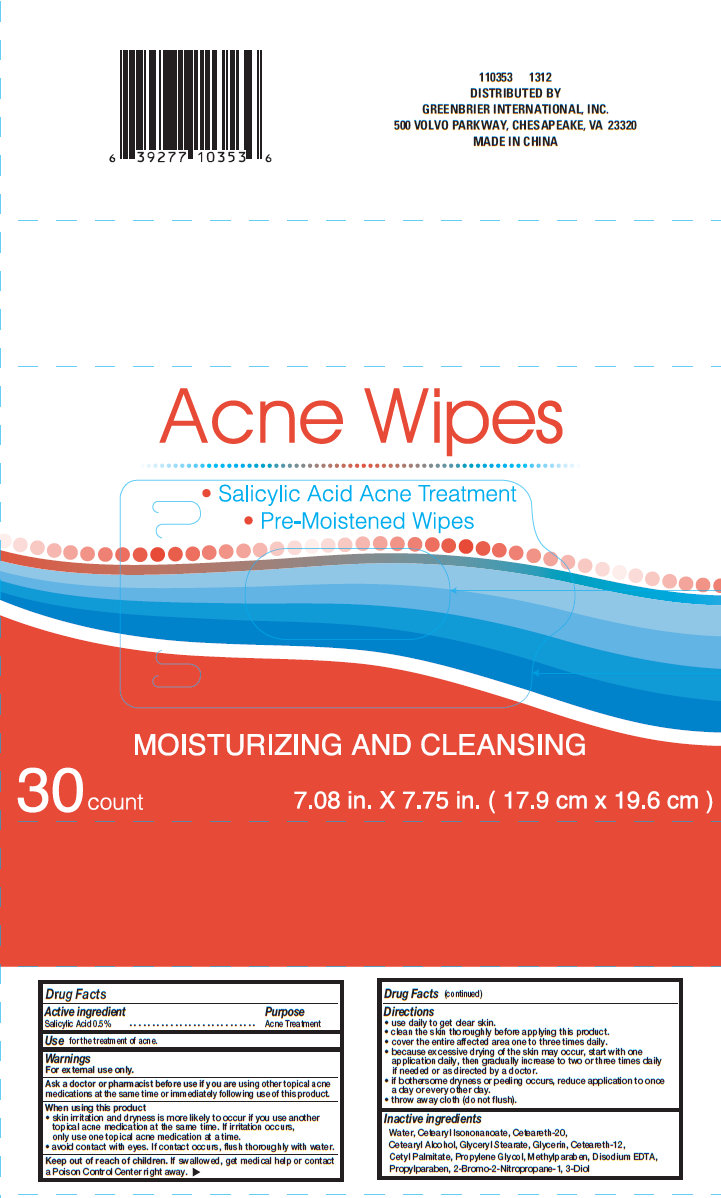 DRUG LABEL: Acne Wipes
NDC: 33992-2150 | Form: SWAB
Manufacturer: Greenbrier International, Inc.
Category: otc | Type: HUMAN OTC DRUG LABEL
Date: 20131010

ACTIVE INGREDIENTS: SALICYLIC ACID 5 mg/1 mL
INACTIVE INGREDIENTS: WATER; CETEARYL ISONONANOATE; POLYOXYL 20 CETOSTEARYL ETHER; CETOSTEARYL ALCOHOL; GLYCERYL MONOSTEARATE; GLYCERIN; CETEARETH-12; CETYL PALMITATE; PROPYLENE GLYCOL; METHYLPARABEN; EDETATE DISODIUM; PROPYLPARABEN

Acne Wipes

Active ingredient

Salicylic Acid 0.5%

Purpose

Acne Treatment

Use

for the treatment of acne.

Warnings

For external use only.

Ask a doctor or pharmacist before use if you are

using other topical acne medications at the same time or immediately following use of this product.

When using this product

- skin irritation and dryness is more likely to occur if you use another topical acne medication at the same time. If irritation occurs, only use one topical medication at a time.
- avoid contact with eyes. If contact occurs, flush thoroughly with water.

Keep out of reach of children.

If swallowed, get medical help or contact a Poison Control Center right away.

Directions

- use daily to get clear skin.
- clean the skin thoroughly before applying this product.
- cover the entire affected area one to three times daily.
- because excessive drying of the skin may occur, start with one application daily, then gradually increase to two or three times daily if needed or as directed by a doctor.
- if bothersome dryness or peeling occurs, reduce application to once a day or every other day.
- throw away cloth (do not flush).

Inactive ingredients

Water, Cetearyl Isononanoate, Ceteareth-20, Cetearyl Alcohol, Glyceryl Stearate, Glycerin, Ceteareth-12, Cetyl Palmitate, Propylene Glycol, Methylparaben, Disodium EDTA, Propylparaben, 2-Bromo-2-Nitropropane-1, 3-Diol